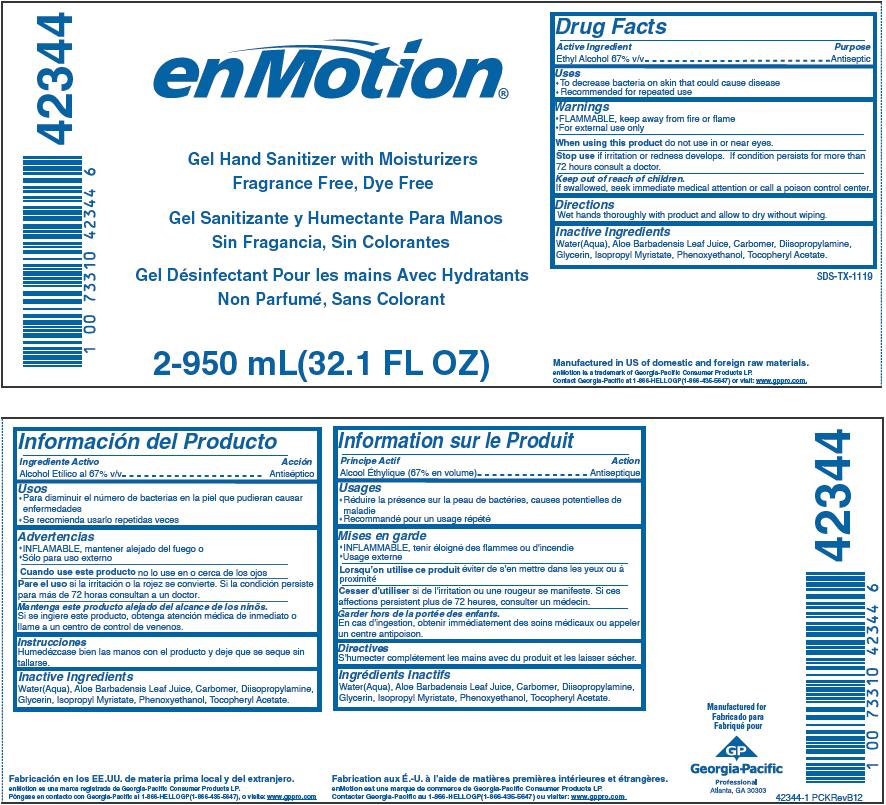 DRUG LABEL: enMotion
NDC: 54622-686 | Form: GEL
Manufacturer: Georgia-Pacific Consumer Products LP
Category: otc | Type: HUMAN OTC DRUG LABEL
Date: 20181231

ACTIVE INGREDIENTS: ALCOHOL 0.5634 g/1 mL
INACTIVE INGREDIENTS: WATER; ALOE VERA LEAF; CARBOMER HOMOPOLYMER TYPE C (ALLYL PENTAERYTHRITOL CROSSLINKED); DIISOPROPYLAMINE; GLYCERIN; ISOPROPYL MYRISTATE; PHENOXYETHANOL; .ALPHA.-TOCOPHEROL ACETATE

enMotion® Gel Hand Sanitizer with Moisturizers, Fragrance Free, Dye Free

Drug Facts

Active Ingredient

Ethyl Alcohol 67% v/v

Purpose

Antiseptic

Uses

- To decrease bacteria on skin that could cause disease
- Recommended for repeated use

Warnings

DO NOT USE

- FLAMMABLE, keep away from fire or flame
- For external use only

When using this product do not use in or near eyes.

Stop use if irritation or redness develops. If condition persists for more than 72 hours consult a doctor.

Keep out of reach of children.

If swallowed, seek immediate medical attention or call a poison control center.

Directions

Wet hands thoroughly with product and allow to dry without wiping.

Inactive Ingredients

Water(Aqua), Aloe Barbadensis Leaf Juice, Carbomer, Diisopropylamine, Glycerin, Isopropyl Myristate, Phenoxyethanol, Tocopheryl Acetate.

Manufactured for
Georgia-Pacific
Professional
Atlanta, GA 30303

PRINCIPAL DISPLAY PANEL - 950 mL Bag Label

42344

enMotion®

Gel Hand Sanitizer with Moisturizers
Fragrance Free, Dye Free

2-950 mL(32.1 FL OZ)